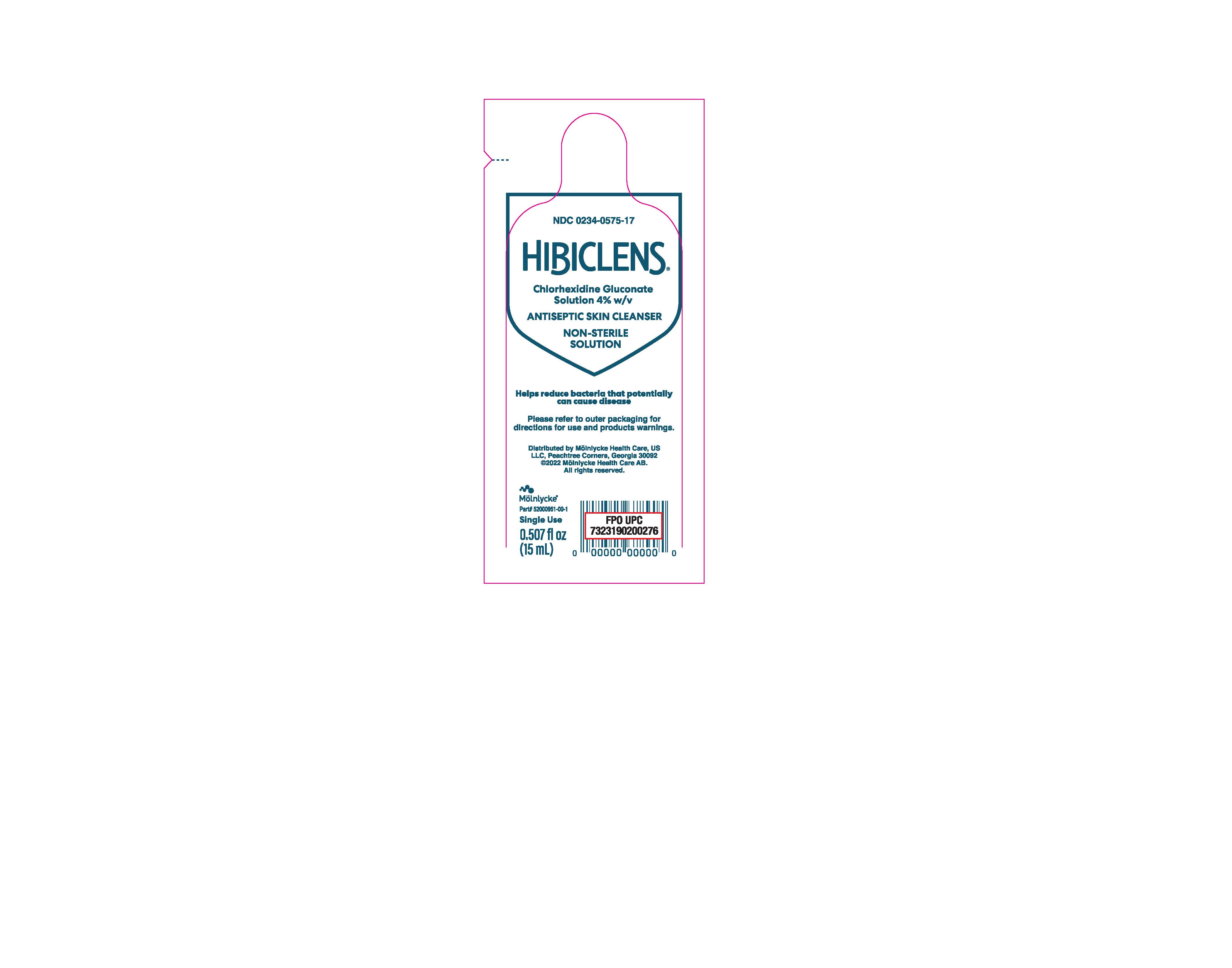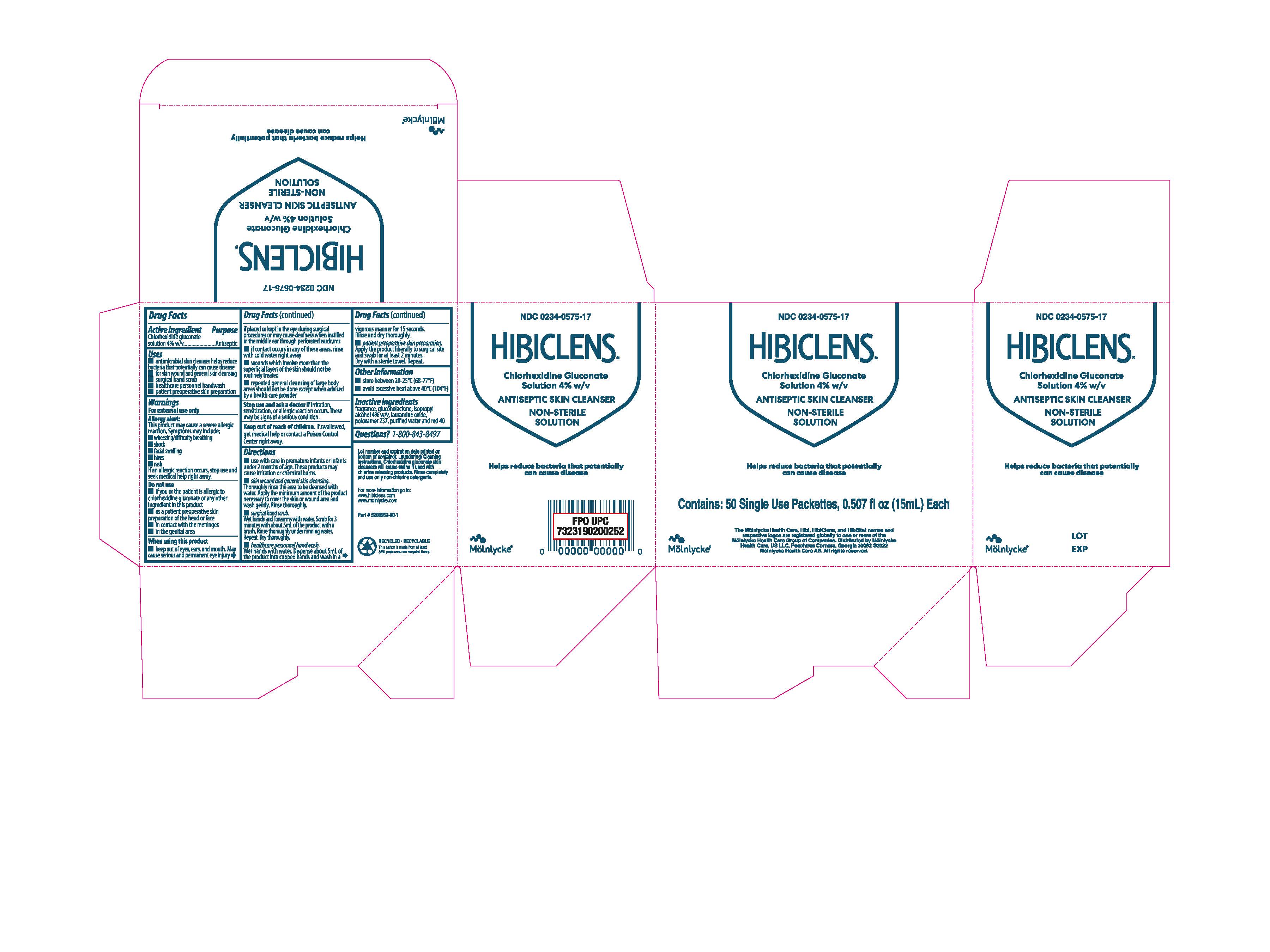 DRUG LABEL: Hibiclens
NDC: 0234-0575 | Form: SOLUTION
Manufacturer: Molnlycke Health Care
Category: otc | Type: HUMAN OTC DRUG LABEL
Date: 20241223

ACTIVE INGREDIENTS: CHLORHEXIDINE GLUCONATE 4 g/100 mL
INACTIVE INGREDIENTS: ISOPROPYL ALCOHOL; WATER; POLOXAMER 237; DIMETHYL LAURAMINE OLEATE; GLUCONOLACTONE; FD&C RED NO. 40

Hibiclens, 4% CHG, packette

ACTIVE INGREDIENT

Chlorhexidine gluconate solution 4.0% w/v

PURPOSE

Antiseptic

Uses

- antimicrobial skin cleanser helps reduce bacteria that potentially can cause disease
- for skin wound and general skin cleansing
- surgical hand scrub
- healthcare personnel handwash
- patient preoperative skin preparation

WARNINGS

For external use only

Allergy alert:

This product may cause a severe allergic reaction. Symptoms may include:

- wheezing/difficulty breathing
- shock
- facial swelling
- hives
- rash

If an allergic reaction occurs, stop use and seek medical help right away.

Do not use

- if you or the patient is allergic to chlorhexidine gluconate or any other ingredient in this product
- as a patient preoperative skin preparation of the head or face
- in contact with the meninges
- in the genital area

When using this product

- keep out of eyes, ears, and mouth. May cause serious and permanent eye injury if places or kept in the eye during surgical procedures or may cause deafness when instilled in the middle ear through perforated eardrums
- if contact occurs in any of these areas, rinse with cold water right away
- wounds which involve more than the superficial layers of the skin should not be routinely treated
- repeated general cleansing of large body areas should not be done except when advised by a health care provider

Stop use and ask a doctor if

irritation, sensitization, or allergic reaction occurs. These may be signs of a serious condition.

Keep out of reach of children

If swallowed, get medical help or contact a Poison Control Center right away.

Directions

- use with care in premature infants or infants under 2 months of age. These products may cause irritation or chemical burns.
- skin wound and general skin cleansing. Thoroughly rinse the area to be cleansed with water. Apply the minimum amount of product necessary to cover the skin or wound area and wash gently. Rinse thoroughly.
- surgical hand scrub. Wet hands and forearms with water. Scrub for 3 minutes with about 5mL of the product with a brush. Rinse thoroughly under running water. Repeat. Dry thoroughly.
- healthcare personnel handwash. Wet hands with water. Dispense about 5mL of the product into cupped hands and wash in a vigorous manner for 15 seconds. Rinse and dry thoroughly.
- patient preoperative skin preparation. Apply the product liberally to surgical site and swab for at least 2 minutes. Dry with a sterile towel. Repeat.

Other information

- store between 20-25°C (68-77°F)
- avoid excessive heat above 40°C (104°F)

INACTIVE INGREDIENT

fragrance, gluconolactone, isopropyl alcohol 4& w/v, lauramine oxide, poloxamer 237, purified water and red 40

Questions?

1-800-843-8497